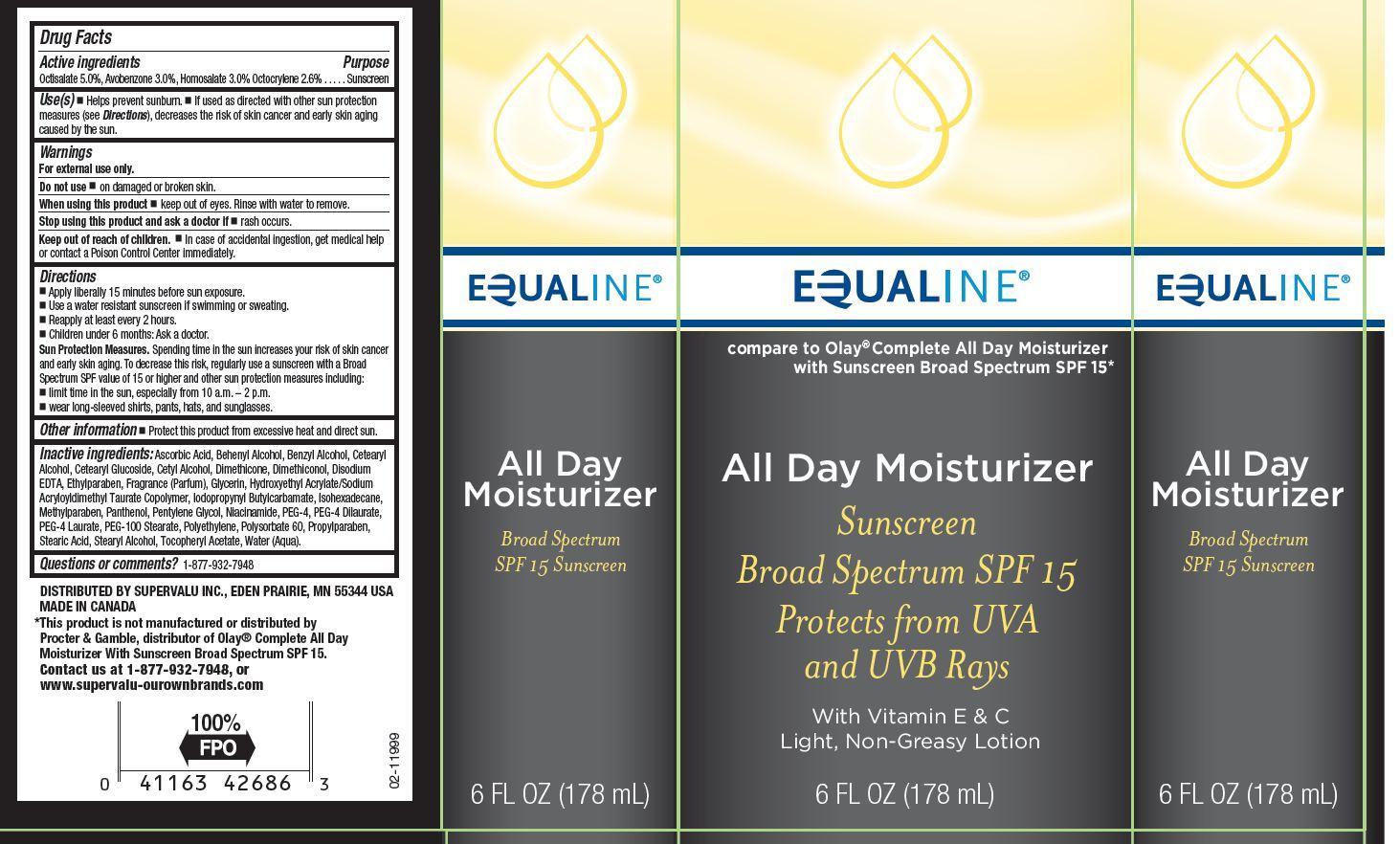 DRUG LABEL: EQUALINE
NDC: 41163-356 | Form: LOTION
Manufacturer: SUPERVALU INC.
Category: otc | Type: HUMAN OTC DRUG LABEL
Date: 20130318

ACTIVE INGREDIENTS: OCTISALATE 50 mg/1 mL; AVOBENZONE 30 mg/1 mL; HOMOSALATE 30 mg/1 mL; OCTOCRYLENE 26 mg/1 mL
INACTIVE INGREDIENTS: ASCORBIC ACID; DOCOSANOL; BENZYL ALCOHOL; CETOSTEARYL ALCOHOL; CETEARYL GLUCOSIDE; CETYL ALCOHOL; DIMETHICONE; DIMETHICONOL (2000 CST); EDETATE DISODIUM; ETHYLPARABEN; GLYCERIN; HYDROXYETHYL ACRYLATE/SODIUM ACRYLOYLDIMETHYL TAURATE COPOLYMER (45000 MPA.S AT 1%); IODOPROPYNYL BUTYLCARBAMATE; ISOHEXADECANE; METHYLPARABEN; PANTHENOL; PENTYLENE GLYCOL; NIACINAMIDE; POLYETHYLENE GLYCOL 200; PEG-4 DILAURATE; PEG-4 LAURATE; PEG-100 STEARATE; HIGH DENSITY POLYETHYLENE; POLYSORBATE 60; PROPYLPARABEN; STEARIC ACID; STEARYL ALCOHOL; .ALPHA.-TOCOPHEROL ACETATE; WATER

DRUG FACTS

ACTIVE INGREDIENTS

OCTISALATE 5.0%, AVOBENZONE 3.0%, HOMOSALATE 3.0%, OCTOCRYLENE 2.6%

PURPOSE

SUNSCREEN

USE(S)

HELPS PREVENT SUNBURN. IF USED AS DIRECTED WITH OTHER SUN PROTECTION MEASURES (SEE DIRECTIONS), DECREASES THE RISK OF SKIN CANCER AND EARLY SKIN AGING CAUSED BY THE SUN.

WARNINGS

FOR EXTERNAL USE ONLY.

DO NOT USE

ON DAMAGED OR BROKEN SKIN.

WHEN USING THIS PRODUCT

KEEP OUT OF EYES. RINSE WITH WATER TO REMOVE.

STOP USING THIS PRODUCT AND ASK A DOCTOR IF

RASH OCCURS.

KEEP OUT OF REACH OF CHILDREN

IN CASE OF ACCIDENTAL INGESTION, GET MEDICAL HELP OR CONTACT A POISON CONTROL CENTER IMMEDIATELY.

DIRECTIONS

APPLY LIBERALLY 15 MINUTES BEFORE SUN EXPOSURE. USE A WATER RESISTANT SUNSCREEN IF SWIMMING OR SWEATING. REAPPLY AT LEAST EVERY 2 HOURS. CHILDREN UNDER 6 MONTHS: ASK A DOCTOR.

SUN PROTECTION MEASURES. SPENDING TIME IN THE SUN INCREASES YOUR RISK OF SKIN CANACER AND EARLY SKIN AGING. TO DECREASE THIS RISK, REGULARLY USE A SUNSCREEN WITH A BROAD SPECTRUM SPF VALUE OF 15 OR HIGHER AND OTHER SUN PROTECTION MEASURES INCLUDING: LIMIT TIME IN THE SUN, ESPECIALLY FROM 10 A.M. - 2 P.M., WEAR LONG-SLEEVED SHIRTS, PANTS, HATS, AND SUNGLASSES.

OTHER INFORMATION

PROTECT THIS PRODUCT FROM EXCESSIVE HEAT AND DIRECT SUN.

INACTIVE INGREDIENTS:

ASCORBIC ACID, BEHENYL ALCOHOL, BENZYL ALCOHOL, CETEARYL ALCOHOL, CETEARYL GLUCOSIDE, CETYL ALCOHOL, DIMETHICONE, DIMETHICONOL, DISODIUM EDTA, ETHYLPARABEN, FRAGRANCE (PARFUM), GLYCERIN, HYDROXYETHYL ACRYLATE/SODIUM ACRYLOYLDIMETHYL TAURATE COPOLYMER, IODOPROPYNYL BUTYLCARBAMATE, ISOHEXADECANE, METHYLPARABEN, PANTHENOL, PENTYLENE GLYCOL, NIACINAMIDE, PEG-4, PEG-4 DILAURATE, PEG-4 LAURATE, PEG-100 STEARATE, POLYETHYLENE, POLYSORBATE 60, PROPYLPARABEN, STEARIC ACID, STEARYL ALCOHOL, TOCOPHERYL ACETATE, WATER (AQUA).

QUESTIONS OR COMMENTS?

1-877-932-7948